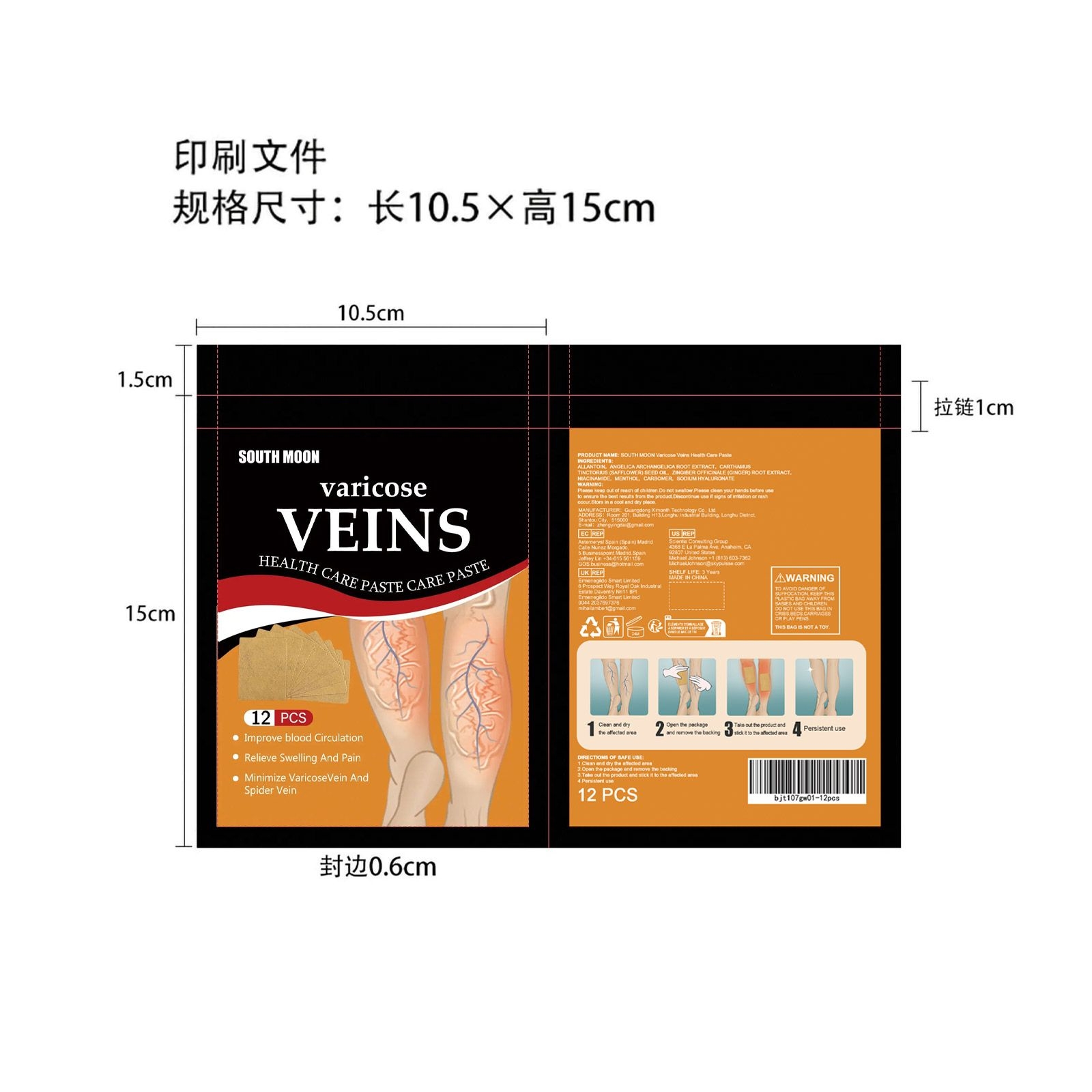 DRUG LABEL: South Moon Health Care
NDC: 84660-028 | Form: PATCH
Manufacturer: Guangdong Ximonth Technology Co., Ltd.
Category: otc | Type: HUMAN OTC DRUG LABEL
Date: 20240926

ACTIVE INGREDIENTS: ANGELICA ARCHANGELICA ROOT 2 g/20 g; SAFFLOWER OIL 3 g/20 g; GINGER 3 g/20 g; NIACINAMIDE 2 g/20 g; MENTHOL 1 g/20 g
INACTIVE INGREDIENTS: HYALURONATE SODIUM 1 g/20 g; ALLANTOIN 6 g/20 g; CARBOMER HOMOPOLYMER, UNSPECIFIED TYPE 2 g/20 g

Active Ingredient(s)

ANGELICA ARCHANGELICA ROOT EXTRACT、CARTHAMUS TINCTORIUS (SAFFLOWER) SEED OIL、ZINGIBER OFFICINALE (GINGER) ROOT EXTRACT、NIACINAMIDE、MENTHOL、CARBOMER

Purpose

Relieve varicose veins

Use

1.Clean and dry the affected area
2.Open the package and remove the backing
3.Take out the product and stick it to the affected area
4.Persistent use

Warnings

Please keep out of reach of children.Do not swallow.Please clean your hands before use to ensure the best results from the product.Discontinue use if signs of irritation or rash occur.Store in a cool and dry place

Do not use

Discontinue use if signs of irritation or rash occur

STOP USE

Discontinue use if signs of irritation or rash occur.

KEEP OUT OF REACH OF CHILDREN

Please keep out of reach of children. Do not swallow.

STORAGE AND HANDLING

Avoid freezing and excessive heat above 40C (104F) ）
Store in a cool and dry place.

INACTIVE INGREDIENT

ALLANTOIN、SODIUM HYALURONATE